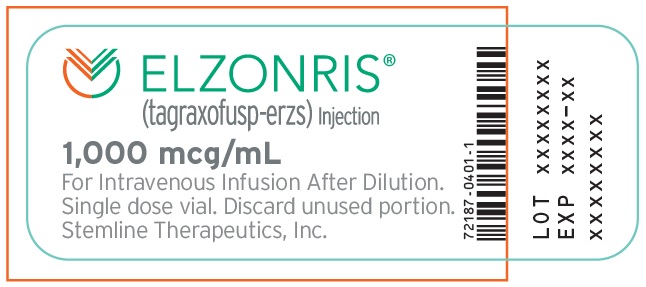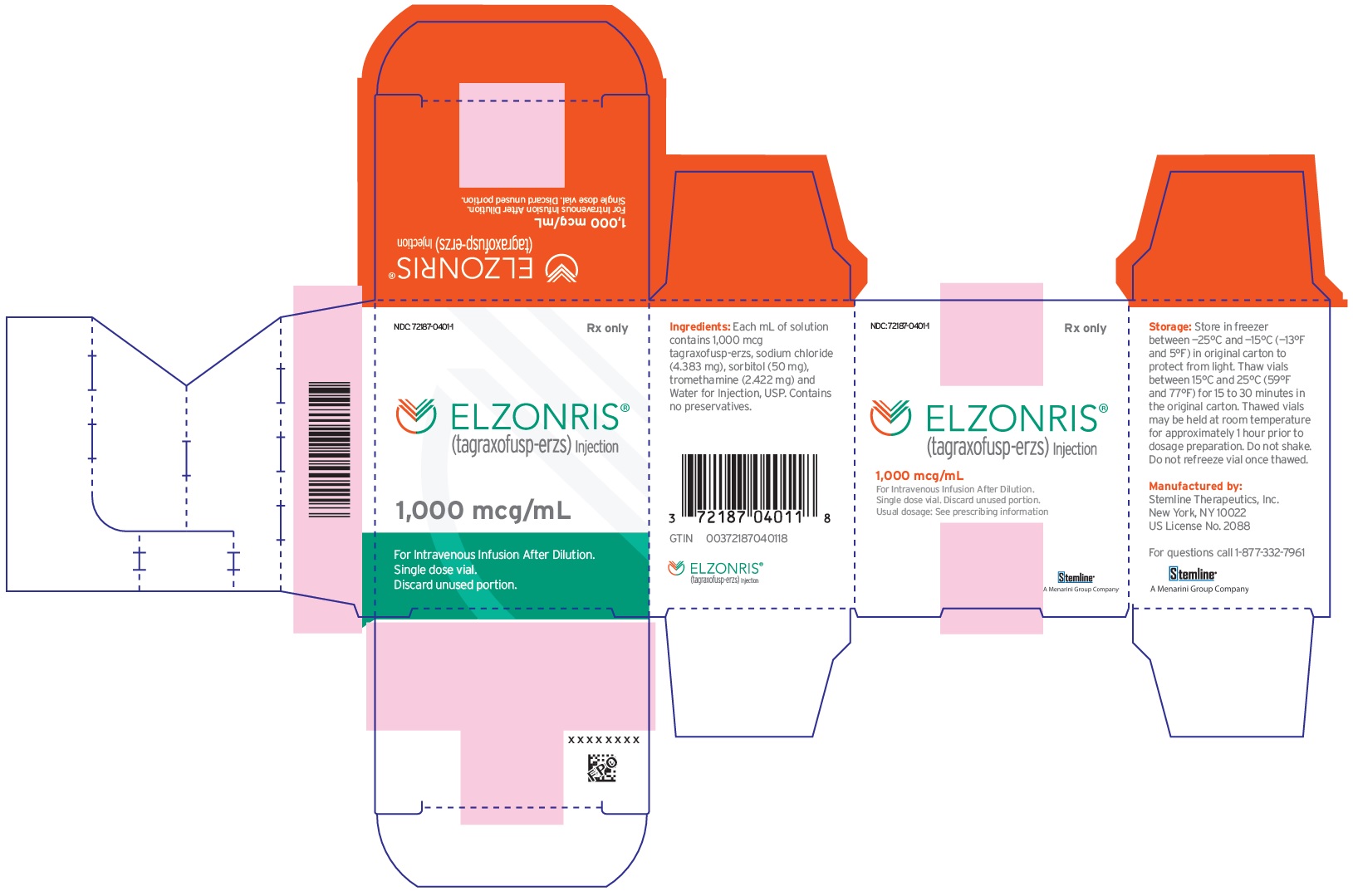 DRUG LABEL: Elzonris
NDC: 72187-0401 | Form: INJECTION, SOLUTION
Manufacturer: Stemline Therapeutics, Inc.
Category: prescription | Type: HUMAN PRESCRIPTION DRUG LABEL
Date: 20241209

ACTIVE INGREDIENTS: TAGRAXOFUSP 1000 ug/1 mL
INACTIVE INGREDIENTS: SODIUM CHLORIDE 4.38 mg/1 mL; SORBITOL 50 mg/1 mL; TROMETHAMINE 2.42 mg/1 mL; WATER

HIGHLIGHTS OF PRESCRIBING INFORMATION

These highlights do not include all the information needed to use
ELZONRIS®safely and effectively. See full prescribing information for
ELZONRIS.
ELZONRIS (tagraxofusp-erzs) injection, for intravenous use
Initial U.S. Approval: 2018

RECENT MAJOR CHANGES

Dosage and Administration, Recommended Dosage (2.1) | 7/2023
Warnings and Precautions, Capillary Leak Syndrome (5.1) | 10/2022
Warnings and Precautions, Hepatotoxicity (5.3) | 10/2022

WARNING: CAPILLARY LEAK SYNDROME

See full prescribing information for complete boxed warning.

Capillary Leak Syndrome (CLS), which may be life-threatening or fatal if not properly managed, can occur in patients receiving ELZONRIS. (5.1)

1 INDICATIONS AND USAGE

ELZONRIS is a CD123-directed cytotoxin indicated for the treatment of blastic plasmacytoid dendritic cell neoplasm (BPDCN) in adults and in pediatric patients 2 years and older (1)

2 DOSAGE AND ADMINISTRATION

- Premedicate with an H1-histamine antagonist, acetaminophen, corticosteroid and H2-histamine antagonist prior to each ELZONRIS infusion. (2.1)
- Administer ELZONRIS intravenously at 12 mcg/kg over 15 minutes once daily on days 1 to 5 of a 21-day cycle. (2.1)
- Administer the first cycle of ELZONRIS in the inpatient setting. Subsequent cycles may be administered in the inpatient or appropriate outpatient setting. (2.1)
- Additional important preparation and administration information is in full prescribing information. See full prescribing information for instructions on preparation and administration. (2.3, 2.4)

3 DOSAGE FORMS AND STRENGTHS

- Injection: 1,000 mcg in 1 mL in a single-dose vial (3)

4 CONTRAINDICATIONS

- None (4)

5 WARNINGS AND PRECAUTIONS

- Hypersensitivity: Monitor patients for signs/symptoms and treat appropriately. (5.2)
- Hepatotoxicity: Monitor ALT and AST. Interrupt ELZONRIS if the transaminases rise to greater than 5 times the upper limit of normal. (5.3)

6 ADVERSE REACTIONS

Most common adverse reactions (incidence ≥ 30%) are capillary leak syndrome, nausea, fatigue, pyrexia, peripheral edema, and weight increase. Most common laboratory abnormalities (incidence ≥ 50%) are decreases in albumin, platelets, hemoglobin, calcium, and sodium, and increases in glucose, ALT and AST. (6.1)

To report SUSPECTED ADVERSE REACTIONS, contact Stemline Therapeutics, Inc. at 1-877-332-7961 or FDA at 1-800-FDA-1088 or www.fda.gov/medwatch.

8 USE IN SPECIFIC POPULATIONS

- Lactation: Advise women not to breastfeed (8.2)

FULL PRESCRIBING INFORMATION

WARNING: CAPILLARY LEAK SYNDROME

Capillary Leak Syndrome (CLS) which may be life-threatening or fatal, can occur in patients receiving ELZONRIS. Monitor for signs and symptoms of CLS and take actions as recommended [see Warnings and Precautions (5.1)].

1 INDICATIONS AND USAGE

ELZONRIS is indicated for the treatment of blastic plasmacytoid dendritic cell neoplasm (BPDCN) in adults and in pediatric patients 2 years and older.

2 DOSAGE AND ADMINISTRATION

2.1 Recommended Dosage

- Administer ELZONRIS at 12 mcg/kg intravenously over 15 minutes once daily on days 1 to 5 of a 21-day cycle. The dosing period may be extended for dose delays up to day 10 of the cycle. Continue treatment with ELZONRIS until disease progression or unacceptable toxicity. The dose is calculated based on the patient’s actual weight.
- Prior to the first dose of the first cycle, ensure serum albumin is greater than or equal to 3.2 g/dL before administering ELZONRIS.
- Premedicate patients with an H1-histamine antagonist (e.g., diphenhydramine hydrochloride), H2-histamine antagonist (e.g., famotidine), corticosteroid (e.g., 50 mg intravenous methylprednisolone or equivalent) and acetaminophen (or paracetamol) approximately 60 minutes prior to each ELZONRIS infusion.
- Administer Cycle 1 of ELZONRIS in the inpatient setting with patient observation through at least 24 hours after the last infusion.
- Administer subsequent cycles of ELZONRIS in the inpatient setting or in a suitable outpatient ambulatory care setting that is equipped with appropriate monitoring for patients with hematopoietic malignancies undergoing treatment. Observe patients for a minimum of 4 hours following each infusion.

2.2 Dosage Modifications

Monitor vital signs and check albumin, transaminases, and creatinine prior to preparing each dose of ELZONRIS. See Table 1 for recommended dose modifications and Table 2 for CLS management guidelines.

Table 1. Recommended ELZONRIS Dosage Modifications
Parameter | Severity Criteria | Dosage Modification
Serum albumin | Serum albumin < 3.5 g/dL or reduced ≥ 0.5 g/dL from value measured prior to initiation of the current cycle | See CLS Management Guidelines (Table 2)
Body weight | Body weight increase ≥ 1.5 kg over pretreatment weight on prior treatment day | See CLS Management Guidelines (Table 2)
Aspartate aminotransferase (AST) or alanine aminotransferase (ALT) | ALT or AST increase > 5 times the upper limit of normal | Withhold ELZONRIS until transaminase elevations are ≤ 2.5 times the upper limit of normal.
Serum creatinine | Serum creatinine > 1.8 mg/dL (159 micromol/L) or creatinine clearance < 60 mL/minute | Withhold ELZONRIS until serum creatinine resolves to ≤ 1.8 mg/dL (159 micromol/L) or creatinine clearance ≥ 60 mL/minute.
Systolic blood pressure | Systolic blood pressure ≥ 160 mmHg or ≤ 80 mmHg | Withhold ELZONRIS until systolic blood pressure is < 160 mmHg or > 80 mmHg.
Heart rate | Heart rate ≥ 130 bpm or ≤ 40 bpm | Withhold ELZONRIS until heart rate is < 130 bpm or > 40 bpm.
Body temperature | Body temperature ≥ 38°C | Withhold ELZONRIS until body temperature is < 38°C.
Hypersensitivity reactions | Mild or moderate | Withhold ELZONRIS until resolution of any mild or moderate hypersensitivity reaction. Resume ELZONRIS at the same infusion rate.
Hypersensitivity reactions | Severe or life-threatening | Discontinue ELZONRIS permanently.

Table 2. CLS Management Guidelines
Time of Presentation | CLS Sign/Symptom | Recommended Action | ELZONRIS Dosing Management
Prior to first dose of ELZONRIS in cycle 1 | Serum albumin < 3.2 g/dL | Administer ELZONRIS when serum albumin ≥ 3.2 g/dL.
During ELZONRIS dosing | Serum albumin < 3.5 g/dL | Administer 25g intravenous albumin (q12h or more frequently as practical) until serum albumin is ≥ 3.5 g/dL AND not more than 0.5 g/dL lower than the value measured prior to dosing initiation of the current cycle. | Interrupt ELZONRIS dosing until the relevant CLS sign/symptom has resolved^1.
During ELZONRIS dosing | Serum albumin reduced by ≥ 0.5 g/dL from the albumin value measured prior to ELZONRIS dosing initiation of the current cycle | Administer 25g intravenous albumin (q12h or more frequently as practical) until serum albumin is ≥ 3.5 g/dL AND not more than 0.5 g/dL lower than the value measured prior to dosing initiation of the current cycle. | Interrupt ELZONRIS dosing until the relevant CLS sign/symptom has resolved^1.
During ELZONRIS dosing | A predose body weight that is increased by ≥ 1.5 kg over the previous day’s predose weight | Administer 25g intravenous albumin (q12h or more frequently as practical), and manage fluid status as indicated clinically (e.g., generally with intravenous fluids and vasopressors if hypotensive and with diuretics if normotensive or hypertensive), until body weight increase has resolved (i.e. the increase is no longer ≥ 1.5 kg greater than the previous day’s predose weight). | Interrupt ELZONRIS dosing until the relevant CLS sign/symptom has resolved^1.
During ELZONRIS dosing | Edema, fluid overload and/or hypotension | Administer 25g intravenous albumin (q12h, or more frequently as practical) until serum albumin is ≥ 3.5 g/dL. Administer 1 mg/kg of methylprednisolone (or an equivalent) per day, until resolution of CLS sign/symptom or as indicated clinically. Aggressive management of fluid status and hypotension if present, which could include intravenous fluids and/or diuretics or other blood pressure management, until resolution of CLS sign/symptom or as clinically indicated. | Interrupt ELZONRIS dosing until the relevant CLS sign/symptom has resolved^1.
^1If ELZONRIS dose is held:
- ELZONRIS administration may resume in the same cycle if all CLS signs/symptoms have resolved and the patient did not require measures to treat hemodynamic instability
- ELZONRIS administration should be held for the remainder of the cycle if CLS signs/symptoms have not resolved or the patient required measures to treat hemodynamic instability (e.g., required administration of intravenous fluids and/or vasopressors to treat hypotension) (even if resolved), and
- ELZONRIS administration may only resume in the next cycle if all CLS signs/symptoms have resolved, and the patient is hemodynamically stable.

2.3 Preparation for Administration

Assure the following components required for dose preparation and administration are available prior to thawing ELZONRIS:

  - One infusion syringe pump
  - One empty 10 mL sterile vial
  - 0.9% Sodium Chloride Injection, USP
  - Three 10 mL sterile syringes
  - One 1 mL sterile syringe
  - One mini-bifuse Y-connector
  - Microbore tubing
  - One 0.2 micron polyethersulfone in-line filter

- Parenteral drug products should be inspected visually for particulate matter and discoloration prior to administration, whenever solution and container permit. Thawed ELZONRIS appearance should be a clear, colorless liquid that may contain a few white to translucent particles.
- Prior to dose preparation thaw at room temperature, between 15°C and 25°C (59°F and 77°F), for 15 to 30 minutes in original carton, and verify thaw visually. Thawed vials may be held at room temperature for approximately 1 hour prior to dosage preparation. Do not force thaw. Do not refreeze vial once thawed.
- Use aseptic technique for preparation of the ELZONRIS dose.
- A 2-step process is required for preparation of the final ELZONRIS dose:
  - Step 1 - Prepare 10 mL of 100 mcg/mL ELZONRIS
    - Using a sterile 10 mL syringe, transfer 9 mL of 0.9% Sodium Chloride Injection, USP to an empty sterile 10 mL vial.
    - Gently swirl the ELZONRIS vial to mix the contents, remove the cap, and using a sterile 1 mL syringe, withdraw 1 mL of thawed ELZONRIS from the product vial.
    - Transfer the 1 mL of ELZONRIS into the 10 mL vial containing the 0.9% Sodium Chloride Injection, USP. Gently invert the vial at least 3 times to mix the contents. Do not shake vigorously.
    - Following dilution the final concentration of ELZONRIS is 100 mcg/mL.
  - Step 2 – Prepare the ELZONRIS infusion set.
    - Calculate the required volume of diluted ELZONRIS (100 mcg/mL) according to patient’s weight.
    - Draw up the required volume into a new syringe (if more than 10 mL of diluted ELZONRIS (100 mcg/mL) is required for the calculated patient dose, repeat step 1 with a second vial of ELZONRIS). Label the ELZONRIS syringe.
    - Prepare a separate syringe with at least 3 mL of 0.9% Sodium Chloride Injection, USP to be used to flush the administration set once the ELZONRIS dose is delivered.
    - Label the 0.9% Sodium Chloride Injection, USP flush syringe.
    - Connect the 0.9% Sodium Chloride Injection, USP flush syringe to one arm of the Y-connector and ensure the clamp is closed.
    - Connect the product syringe to the other arm of the Y-connector and ensure the clamp is closed.
    - Connect the terminal end of the Y-connector to the microbore tubing.
    - Remove the cap from the supply side of the 0.2 micron filter and attach it to the terminal end of the microbore tubing.
    - Unclamp the arm of the Y-connector connected to the 0.9% Sodium Chloride Injection, USP flush syringe. Prime the Y-connector up to the intersection (do not prime the full infusion set with 0.9% Sodium Chloride Injection, USP). Re-clamp the Y-connector line on the 0.9% Sodium Chloride Injection, USP flush arm.
    - Remove the cap on the terminal end of the 0.2 micron filter and set it aside. Unclamp the arm of the Y-connector connected to the product syringe, and prime the entire infusion set, including the filter. Recap the filter, and re-clamp the Y-connector line on the product side. The infusion set is now ready for delivery for dose administration.
- Administer ELZONRIS within 4 hours. During this 4-hour window, the prepared dose should remain at room temperature.
- Do not reuse excess ELZONRIS. Any excess material should be thrown away immediately following infusion.

2.4 Administration

- Establish venous access and maintain with sterile 0.9% Sodium Chloride Injection, USP.
- Administer the prepared ELZONRIS dose via infusion syringe pump over 15 minutes. The total infusion time will be controlled using a syringe pump to deliver the entire dose and the 0.9% Sodium Chloride Injection, USP flush over 15 minutes.
- Insert the ELZONRIS syringe into the syringe pump, open the clamp on the ELZONRIS side of the Y-connector and deliver the prepared ELZONRIS dose.
- Once the ELZONRIS syringe has been emptied, remove it from the pump and place the 0.9% Sodium Chloride Injection, USP flush syringe in the syringe pump.
- Open the clamp on the 0.9% Sodium Chloride Injection, USP flush side of the Y-connector and resume infusion via the syringe pump at the pre-specified flow to push remaining ELZONRIS dose out of the infusion line to complete delivery.

3 DOSAGE FORMS AND STRENGTHS

Injection: 1,000 mcg in 1 mL clear colorless solution in a single-dose vial.

4 CONTRAINDICATIONS

None.

5 WARNINGS AND PRECAUTIONS

5.1 Capillary Leak Syndrome

Capillary leak syndrome (CLS), including life-threatening and fatal cases, has been reported among patients treated with ELZONRIS. In patients receiving ELZONRIS in clinical trials, the overall incidence of CLS was 53% (65/122), including Grade 1 or 2 in 43% (52/122) of patients, Grade 3 in 7% (8/122) of patients, Grade 4 in 1% (1/122) of patients, and four fatalities (3%) [see Adverse Reactions (6.1)]. The median time to onset was 4 days (range - 1 to 46 days), and all but 5 patients experienced an event in Cycle 1.

Before initiating therapy with ELZONRIS, ensure that the patient has adequate cardiac function and serum albumin is greater than or equal to 3.2 g/dL. During treatment with ELZONRIS, monitor serum albumin levels prior to the initiation of each dose of ELZONRIS and as indicated clinically thereafter, and assess patients for other signs or symptoms of CLS, including weight gain, new onset or worsening edema, including pulmonary edema, hypotension or hemodynamic instability [see Dosage and Administration (2.2)].

5.2 Hypersensitivity Reactions

ELZONRIS can cause severe hypersensitivity reactions. In patients receiving ELZONRIS in clinical trials, hypersensitivity reactions were reported in 43% (53/122) of patients treated with ELZONRIS and were Grade ≥ 3 in 7% (9/122) [see Adverse Reactions (6.1)]. Manifestations of hypersensitivity reported in ≥ 5% of patients include rash, pruritus, and stomatitis. Monitor patients for hypersensitivity reactions during treatment with ELZONRIS. Interrupt ELZONRIS infusion and provide supportive care as needed if a hypersensitivity reaction should occur [see Dosage and Administration (2.2)].

5.3 Hepatotoxicity

Treatment with ELZONRIS was associated with elevations in liver enzymes. In patients receiving ELZONRIS in clinical trials, elevations in ALT occurred in 79% (96/122) and elevations in AST occurred in 76% (93/122) [see Adverse Reactions (6.1)]. Grade 3 ALT elevations were reported in 26% (32/122) of patients. Grade 3 AST elevations were reported in 30% (36/122) and Grade 4 AST elevations were reported in 3% (4/122) of patients. Elevated liver enzymes occurred in the majority of patients in Cycle 1 and were reversible following dose interruption.

Monitor alanine aminotransferase (ALT) and aspartate aminotransferase (AST) prior to each infusion with ELZONRIS. Withhold ELZONRIS temporarily if the transaminases rise to greater than 5 times the upper limit of normal and resume treatment upon normalization or when resolved [see Dosage and Administration (2.2)].

6 ADVERSE REACTIONS

The following serious adverse drug reactions are described elsewhere in the labeling:

- Capillary Leak Syndrome [see Warnings and Precautions (5.1)]
- Hypersensitivity Reactions [see Warnings and Precautions (5.2)]
- Hepatotoxicity [see Warnings and Precautions (5.3)]

6.1 Clinical Trials Experience

Because clinical trials are conducted under widely varying conditions, adverse reaction rates observed in the clinical trials of a drug cannot be directly compared to rates in the clinical trials of another drug and may not reflect the rates observed in practice.

Safety of ELZONRIS was assessed in a single-arm clinical trial that included 122 adults with newly diagnosed or relapsed/refractory myeloid malignancies, including 86 with BPDCN, treated with ELZONRIS 12 mcg/kg daily for 5 days of a 21-day cycle. The overall median number of cycles started was 2.5 (range, 1-76), and 4 in patients with BPDCN (range, 1-76).

Four (3%) patients (4/122) had fatal adverse reactions, all of which were related to capillary leak syndrome. Overall, 8% (10/122) of patients discontinued treatment with ELZONRIS due to an adverse reaction; the most common adverse reactions resulting in treatment discontinuation were hepatic toxicities, hypoalbuminemia and CLS (2% each).

Table 3 summarizes the common (≥ 10%) adverse reactions with ELZONRIS in patients with myeloid malignancies. The rate of any given adverse reaction or lab abnormality was derived from all the reported events of that type.

Table 3. Adverse Reactions in ≥ 10% of Patients Receiving 12 mcg/kg of ELZONRIS
 | N=122
 | All Grades % | Grade ≥ 3 %
Vascular disorders
Capillary leak syndrome^1 | 53 | 11
Hypotension | 25 | 7
Hypertension | 14 | 6
General disorders and administration site conditions
Fatigue | 45 | 7
Pyrexia | 43 | 0
Peripheral edema | 39 | 1
Chills | 26 | 1
Gastrointestinal disorders
Nausea | 45 | 0
Constipation | 24 | 0
Diarrhea | 21 | 0
Vomiting | 19 | 0
Investigations
Weight increase | 31 | 0
Nervous system disorders
Headache | 28 | 0
Dizziness | 21 | 0
Metabolism and nutrition disorders
Decreased appetite | 22 | 0
Respiratory, thoracic and mediastinal disorders
Dyspnea | 20 | 3
Epistaxis | 12 | 1
Cough | 12 | 0
Blood and lymphatic system disorders
Febrile neutropenia | 19 | 16
Musculoskeletal and connective tissue disorders
Back pain | 19 | 2
Pain in extremity | 10 | 2
Cardiac disorders
Tachycardia | 17 | 0
Psychiatric disorders
Insomnia | 16 | 0
Anxiety | 15 | 0
Skin and subcutaneous tissue disorders
Pruritus | 10 | 0
^1 Capillary leak syndrome defined as any event reported as CLS during treatment with ELZONRIS or the occurrence of at least 2 of the following CLS manifestations within 7 days of each other: hypoalbuminemia (including albumin value less than 3.0 g/dL), edema (including weight increase of 5 kg or more), hypotension (including systolic blood pressure less than 90 mmHg).

Clinically relevant adverse reactions occurring in less than 10% of patients treated with ELZONRIS included tumor lysis syndrome.

Table 4 summarizes the clinically important laboratory abnormalities that occurred in ≥ 10% patients with myeloid malignancies treated with ELZONRIS.

Table 4. Selected Laboratory Abnormalities in Patients Receiving 12 mcg/kg of ELZONRIS
 | Treatment-Emergent Laboratory Abnormalities
 | All Grades % | Grade ≥ 3 %
Hematology
Platelets decrease | 68 | 49
Hemoglobin decrease | 61 | 30
Neutrophils decrease | 38 | 29
Chemistry
Glucose increase | 89 | 21
ALT increase | 79 | 26
AST increase | 76 | 33
Albumin decrease | 72 | 1
Calcium decrease | 57 | 2
Sodium decrease | 52 | 9
Potassium decrease | 36 | 6
Phosphate decrease | 32 | 10
Creatinine increase | 26 | 0
Magnesium decrease | 25 | 0
Alkaline phosphatase increase | 22 | 1
Potassium increase | 20 | 3
Magnesium increase | 13 | 4
Bilirubin increase | 11 | 0
Glucose decrease | 10 | 0

8 USE IN SPECIFIC POPULATIONS

8.1 Pregnancy

Risk Summary

Based on its mechanism of action, ELZONRIS has the potential for adverse effects on embryo-fetal development [see Clinical Pharmacology (12.1)]. There are no available data on ELZONRIS use in pregnant women to inform a drug-associated risk of adverse developmental outcomes. Animal reproduction or developmental toxicity studies have not been conducted with tagraxofusp-erzs. Advise pregnant women of the potential risk to the fetus.

The estimated background risk of major birth defects and miscarriage for the indicated population is unknown. All pregnancies have a risk of birth defect, loss, or other adverse outcomes. In the US general population, the estimated background risk of major birth defects and miscarriage in clinically recognized pregnancies is 2% to 4%, and 15% to 20%, respectively.

8.2 Lactation

Risk Summary

No data are available regarding the presence of ELZONRIS in human milk, the effects on the breastfed child, or the effects on milk production. Because of the potential for serious adverse reactions in breastfed children from ELZONRIS, breast feeding is not recommended during treatment and for 1 week after the last dose.

8.3 Females and Males of Reproductive Potential

Based on its mechanism of action, ELZONRIS may cause fetal harm when administered to a pregnant woman [see Use in Specific Populations (8.1)]

Pregnancy Testing:

Conduct pregnancy testing in females of reproductive potential within 7 days prior to initiating ELZONRIS treatment.

Contraception:

Advise females to use acceptable contraceptive methods during ELZONRIS treatment and for 1 week after the last dose of ELZONRIS.

8.4 Pediatric Use

The safety and effectiveness of ELZONRIS for treatment of BPDCN have been established in pediatric patients 2 years of age and older (no data for pediatric patients less than 2 years of age). Use of ELZONRIS in these age groups is supported by evidence from an adequate and well-controlled study of ELZONRIS in adults with BPDCN and additional safety data from three pediatric patients with BPDCN, including 1 child (2 years to < 12 years old) and 2 adolescents (12 years to < 17 years old), treated with ELZONRIS at the recommended dosage. The safety profile of ELZONRIS in the pediatric patients was similar to that seen in the adults. Efficacy for pediatric patients is extrapolated from the results of STML-401-0114 [see Clinical Studies 14.1, 14.2]. Safety and effectiveness have not been established in pediatric patients younger than 2 years of age.

8.5 Geriatric Use

Of the 86 patients who received ELZONRIS for BPDCN at the labeled dose in STML-401-0114, 63% were 65 years and older and 22% were 75 years and older. Patients 75 years or older experienced a higher incidence of altered mental status (including confusional state, delirium, mental status changes, dementia, and encephalopathy) than patients under 75 years of age.

11 DESCRIPTION

Tagraxofusp-erzs, a CD123-directed cytotoxin, is a fusion protein comprised of a recombinant human interleukin-3 (IL-3) and truncated diphtheria toxin (DT). Tagraxofusp-erzs has an approximate molecular weight of 57,695 Daltons. Tagraxofusp-erzs is constructed by recombinant DNA technology and produced in Escherichia coli cells.

ELZONRIS (tagraxofusp-erzs) injection is a preservative-free, sterile, clear, colorless solution that may contain a few white to translucent particles and requires dilution prior to intravenous infusion. ELZONRIS is supplied at a concentration of 1,000 mcg/mL in a single-dose vial. Each mL of ELZONRIS contains 1,000 mcg tagraxofusp-erzs, sodium chloride (4.38 mg), sorbitol (50 mg), tromethamine (2.42 mg) and Water for Injection, USP and pH is 7.5.

12 CLINICAL PHARMACOLOGY

12.1 Mechanism of Action

Tagraxofusp-erzs is a CD123-directed cytotoxin composed of recombinant human interleukin-3 (IL-3) and truncated diphtheria toxin (DT) fusion protein that inhibits protein synthesis and causes cell death in CD123-expressing cells.

12.2 Pharmacodynamics

The exposure-response relationships and the time course of pharmacodynamic response for ELZONRIS have not been fully characterized.

12.3 Pharmacokinetics

Following administration of tagraxofusp-erzs 12 mcg/kg via 15-minute infusion in patients with BPDCN, the mean (SD) area under the plasma drug concentration over time curve (AUC) was 231 (123) hr·mcg/L and maximum plasma concentration (Cmax) was 162 (58.1) mcg/L.

Distribution
Mean (SD) volume of distribution of tagraxofusp-erzs is 5.1 (1.9) L in patients with BPDCN.

Elimination
Mean (SD) clearance is 7.1 (7.2) L/hr in patients with BPDCN. Mean (SD) terminal half-life of tagraxofusp-erzs is 0.7 (0.3) hours.

Specific Population
No clinically significant differences in the pharmacokinetics of tagraxofusp-erzs were observed based on age (22 to 84 years), sex, mild to moderate renal impairment (eGFR 30 to 89 mL/min/1.73 m^2, estimated by MDRD), mild (total bilirubin ≤ ULN and AST >ULN, or total bilirubin 1 to 1.5 times ULN and any AST) or moderate (total bilirubin >1.5 to 3 times ULN and any AST) hepatic impairment or body weight after adjusting dose by body weight. The effect of severe renal impairment (eGFR 15 to 29 mL/min/1.73 m^2), or severe hepatic impairment (total bilirubin >3 times ULN and any AST) on tagraxofusp-erzs pharmacokinetics is unknown.

Drug Interaction Studies
No drug-drug interaction studies have been conducted with ELZONRIS.

12.6 Immunogenicity

The detection of antibody formation is highly dependent on the sensitivity and specificity of the assay. Additionally, the observed incidence of antibody (including neutralizing antibody) positivity in an assay may be influenced by several factors including assay methodology, sample handling, timing of sample collection, concomitant medications, and underlying disease. For these reasons, comparison of the incidence of antibodies to ELZONRIS with the incidences of antibodies to other products may be misleading. Immune response to ELZONRIS was evaluated by assessment of serum binding reactivity against ELZONRIS (anti-drug antibodies; ADA) and neutralizing antibodies by inhibition of functional activity. Immune response to ELZONRIS was assessed using two immunoassays. The first assay detected reactivity directed against ELZONRIS (ADA), and the second assay detected reactivity against the interleukin-3 (IL-3) portion of ELZONRIS. Two cell-based assays were used to investigate the presence of neutralizing antibodies by inhibition of a cell-based functional activity.

In 130 patients treated with ELZONRIS in 4 clinical trials:

- 96% (115/120) of patients evaluable for the presence of pre-existing ADA at baseline before treatment were confirmed positive with 21% being positive for the presence of neutralizing antibodies. The high prevalence of ADA at baseline was anticipated due to diphtheria immunization.
- 99% (107/108) of patients evaluable for treatment-emergent ADA tested positive with most patients showing an increase in ADA titer by the end of Cycle 2 of ELZONRIS.
- 85% (86/101) of ADA-positive patients evaluable for the presence of neutralizing antibodies were neutralizing antibody-positive.
- 68% (73/108) of patients evaluable for treatment-emergent anti-IL-3 antibodies tested positive with most patients testing positive by Cycle 3 of ELZONRIS.

Anti-Product Antibody Effects on Pharmacokinetics
The presence of ADA had a clinically significant effect on the pharmacokinetics of tagraxofusp-erzs. Pharmacokinetic data obtained following doses given in Cycle 3 showed increased titers of anti-drug antibodies and reduced free ELZONRIS concentration in most plasma samples. Following administration of tagraxofusp-erzs 12 mcg/kg via 15-minute infusion in patients with pre-existing anti-drug antibodies, the mean (SD) volume of distribution of tagraxofusp-erzs is 21.2 (25.4) L, clearance is 13.9 (19.4) L/hr, AUC is 151 (89.2) hr·mcg/L and Cmax is 80.0 (82.2) mcg/L.

13 NONCLINICAL TOXICOLOGY

13.1 Carcinogenesis, Mutagenesis, Impairment of Fertility

No studies have been conducted to assess the carcinogenic or genotoxic potential of tagraxofusp. Animal fertility studies have not been conducted with tagraxofusp-erzs.

13.2 Animal Toxicology and/or Pharmacology

At human equivalent doses greater than or equal to 1.6 times the recommended dose based on body surface area, severe kidney tubular degeneration/necrosis was observed in cynomolgus monkeys. At human equivalent doses equal to the recommended dose, degeneration/necrosis of the choroid plexus in the brain was observed in cynomolgus monkeys. The reversibility of this finding was not assessed at lower doses, but the finding was irreversible and became progressively more severe at a human equivalent dose 1.6 times the recommended dose, 3 weeks after dosing stopped.

14 CLINICAL STUDIES

14.1 First-Line Treatment of Blastic Plasmacytoid Dendritic Cell Neoplasm (BPDCN)

STML-401-0114 (NCT 02113982; Study 0114) was a multicenter, open-label, single-arm, clinical trial that included a prospective cohort of 13 patients with treatment-naive BPDCN. Treatment consisted of ELZONRIS 12 mcg/kg intravenously over 15 minutes once daily on days 1 to 5 of a 21-day cycle. Patient baseline characteristics are presented in Table 5.

Table 5. Baseline Demographics of Patients with Treatment-Naive BPDCN
Parameter | N=13
Gender, N (%)
Male | 11 (84.6)
Female | 2 (15.4)
Age (years), N (%)
Median | 65.0
Minimum, Maximum | 22, 84
ECOG, N (%)
0 | 8 (61.5)
1 | 5 (38.5)
BPDCN at Baseline, N (%)
Skin | 13 (100.0)
Bone Marrow | 7 (53.8)
Peripheral Blood | 3 (23.1)
Lymph Nodes | 6 (46.2)
Viscera | 2 (15.4)

The efficacy of ELZONRIS in patients with treatment-naive BPDCN was based on the rate of complete response or clinical complete response (CR/CRc). Key efficacy measures are presented in Table 6. The median time to CR/CRc was 57 days (range: 14 to 107).

Table 6. Efficacy Measures in Patients with Treatment-Naive BPDCN
Parameter | N=13
CR/CRc* Rate, N (%) | 7 (53.8)
(95% CI) | (25.1, 80.8)
Duration of CR/CRc (months)
Median | Not reached
Minimum, Maximum | 3.9, 12.2
Duration of follow up (months)
Median | 11.5
Minimum, Maximum | 0.2, 12.7
* CRc is defined as complete response with residual skin abnormality not indicative of active disease.

14.2 Relapsed or Refractory Blastic Plasmacytoid Dendritic Cell Neoplasm (BPDCN)

STML-401-0114 (NCT02113982; Study 0114) was a multicenter, open-label, single-arm, clinical trial that included 15 patients with relapsed or refractory BPDCN. Treatment consisted of ELZONRIS 12 mcg/kg on days 1 to 5 of each 21-day cycle. Patient baseline characteristics are presented in Table 7.

Table 7. Baseline Demographics of Patients with Relapsed or Refractory BPDCN
Parameter | N=15
Gender, N (%)
Male | 13 (86.7)
Female | 2 (13.3)
Age (years)
Median | 72
Minimum, Maximum | 44, 80
ECOG, N (%)
0 | 5 (33.3)
1 | 10 (66.7)
BPDCN at Baseline, N (%)
Skin | 13 (86.7)
Bone marrow | 9 (60.0)
Lymph node | 8 (53.3)
Visceral | 4 (26.7)
Peripheral blood | 1 (6.7)

In the 15 patients with relapsed/refractory BPDCN, one patient achieved a CR (duration: 111 days) and one patient achieved a CRc (duration: 424 days).

16 HOW SUPPLIED/STORAGE AND HANDLING

How Supplied

ELZONRIS (tagraxofusp-erzs) injection is a preservative-free, sterile, clear, colorless, 1,000 mcg in 1 mL solution supplied in a single-dose glass vial. Each carton contains one vial (NDC 72187-0401-1).

Storage and Handling

Store in freezer between -25°C and -15°C (-13°F and 5°F). Protect ELZONRIS from light by storing in the original package until time of use. Thaw vials at room temperature between 15°C and 25°C (59°F and 77°F) prior to preparation [see Dosage and Administration (2.3)]. Do not refreeze the vial once thawed. Do not use beyond expiration date on container.

17 PATIENT COUNSELING INFORMATION

Capillary Leak Syndrome

Advise patients of the risk of capillary leak syndrome (CLS), and to contact their health care professional for signs and symptoms associated with CLS including new or worsening edema, weight gain, shortness of breath, and/or hypotension after infusion. Advise patients to weigh themselves daily [see Warnings and Precautions (5.1)].

Hypersensitivity

Advise patients of the risk of hypersensitivity reactions, and to contact their healthcare professional for signs and symptoms associated with hypersensitivity reactions including rash, flushing, wheezing and swelling of the face [see Warnings and Precautions (5.2)].

Hepatotoxicity

Advise patients to report symptoms that may indicate elevated liver enzymes including fatigue, anorexia and/or right upper abdominal discomfort [see Warnings and Precautions (5.3)].

Contraception

Advise females to avoid pregnancy and to use acceptable contraceptive methods during ELZONRIS treatment and for 1 week after the last dose of ELZONRIS [see Use in Specific Populations (8.3)].

Lactation

Advise women not to breastfeed [see Use in Specific Populations (8.2)].

Manufactured by:
Stemline Therapeutics, Inc.
New York, NY 10022
US License No. 2088

Stemline®
A Menarini Group Company